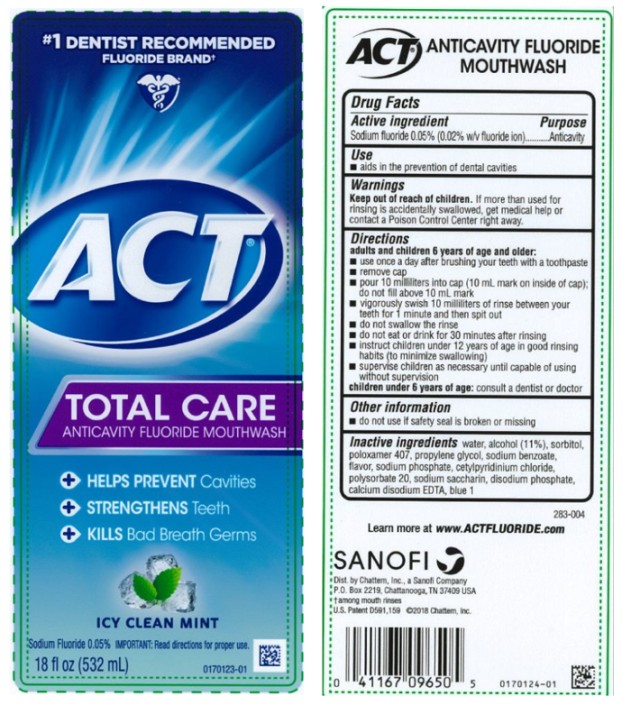 DRUG LABEL: ACT Total Care Anticavity Fluoride Icy Clean Mint
NDC: 41167-0965 | Form: MOUTHWASH
Manufacturer: Chattem, Inc.
Category: otc | Type: HUMAN OTC DRUG LABEL
Date: 20260112

ACTIVE INGREDIENTS: SODIUM FLUORIDE 0.2 mg/1 mL
INACTIVE INGREDIENTS: WATER; ALCOHOL; SORBITOL; POLOXAMER 407; PROPYLENE GLYCOL; SODIUM BENZOATE; SODIUM PHOSPHATE; CETYLPYRIDINIUM CHLORIDE; POLYSORBATE 20; SACCHARIN SODIUM; EDETATE CALCIUM DISODIUM ANHYDROUS; FD&C BLUE NO. 1

ACT Total Care Anticavity Fluoride Mouthwash Icy Clean Mint

Drug Facts

Active ingredient

Sodium fluoride 0.05% (0.02% w/v fluoride ion)

Purpose

Anticavity

Use

- aids in the prevention of dental cavities

Warnings

Keep out of reach of children.

If more than used for rinsing is accidentally swallowed, get medical help or contact a Poison Control Center right away.

Directions

adults and children 6 years of age and older:

- use once a day after brushing your teeth with a toothpaste
- remove cap
- pour 10 milliliters into cap (10 mL mark on inside of cap); do not fill above 10 mL mark
- vigorously swish 10 milliliters of rinse between your teeth for 1 minute and then spit out
- do not swallow the rinse
- do not eat or drink for 30 minutes after rinsing
- instruct children under 12 years of age in good rinsing habits (to minimize swallowing)
- supervise children as necessary until capable of using without supervision

children under 6 years of age: consult a dentist or doctor

Other information

- do not use if safety seal is broken or missing

Inactive ingredients

water, alcohol (11%), sorbitol, poloxamer 407, propylene glycol, sodium benzoate, flavor, sodium phosphate, cetylpyridinium chloride, polysorbate 20, sodium saccharin, disodium phosphate, calcium disodium EDTA, blue 1 (283-004)

www.actfluoride.com

PRINCIPAL DISPLAY PANEL

#1 DENTIST RECOMMENDED
FLUORIDE BRAND

ACT®
TOTAL CARE
ANTICAVITY FLUORIDE
MOUTHWASH

ICY CLEAN MINT
Sodium Fluoride 0.05%
18 fl oz (532 mL)